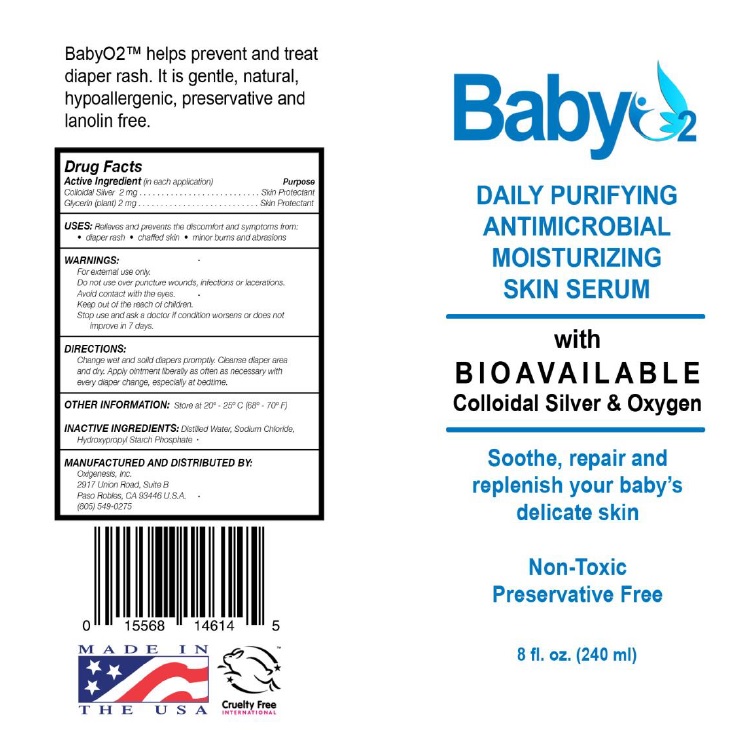 DRUG LABEL: BabyO2
NDC: 72136-005 | Form: SOLUTION
Manufacturer: Oxigenesis, Inc.
Category: otc | Type: HUMAN OTC DRUG LABEL
Date: 20190226

ACTIVE INGREDIENTS: SILVER 2 mg/240 mL; GLYCERIN 2 mg/240 mL
INACTIVE INGREDIENTS: WATER; SODIUM CHLORIDE NA-22; HYDROXYPROPYL CORN STARCH (5% SUBSTITUTION BY WEIGHT)

BabyO2™

Active ingredients Purpose

Colloidal Silver 2 mg ................................................ Skin Protectant

Glycerin (Plant) 2 mg................................................ Skin Protectant

Uses

Relieves and prevents the discomfort and symptoms from: diaper rash, chaffed skin, minor burns and abrasions.

Warnings

For external use only.

Do not use over puncture wounds, infections or lacerations.

Avoid contact with the eyes.

Stop use and ask a doctor if condition worsens or does not improve in 7 days.

Keep out of reach of children.

Directions

Change wet and solid diapers promptly. Cleanse diaper area and dry. Apply ointment liberally as often necessary with every diaper change, especially at bedtime.

Other information

Sstore at 20°-25°C (68° -70° F)

Inactive ingredients

Distilled water, Sodium Chloride, Hydroxypropyl Starch Phosphate.

DOSAGE AND ADMINISTRATION

Marketed & Distributed by:

Oxigenesis, Inc.
2917 Union Road, Suite B
Paso Robles, CA 93446 USA
805-549-0275